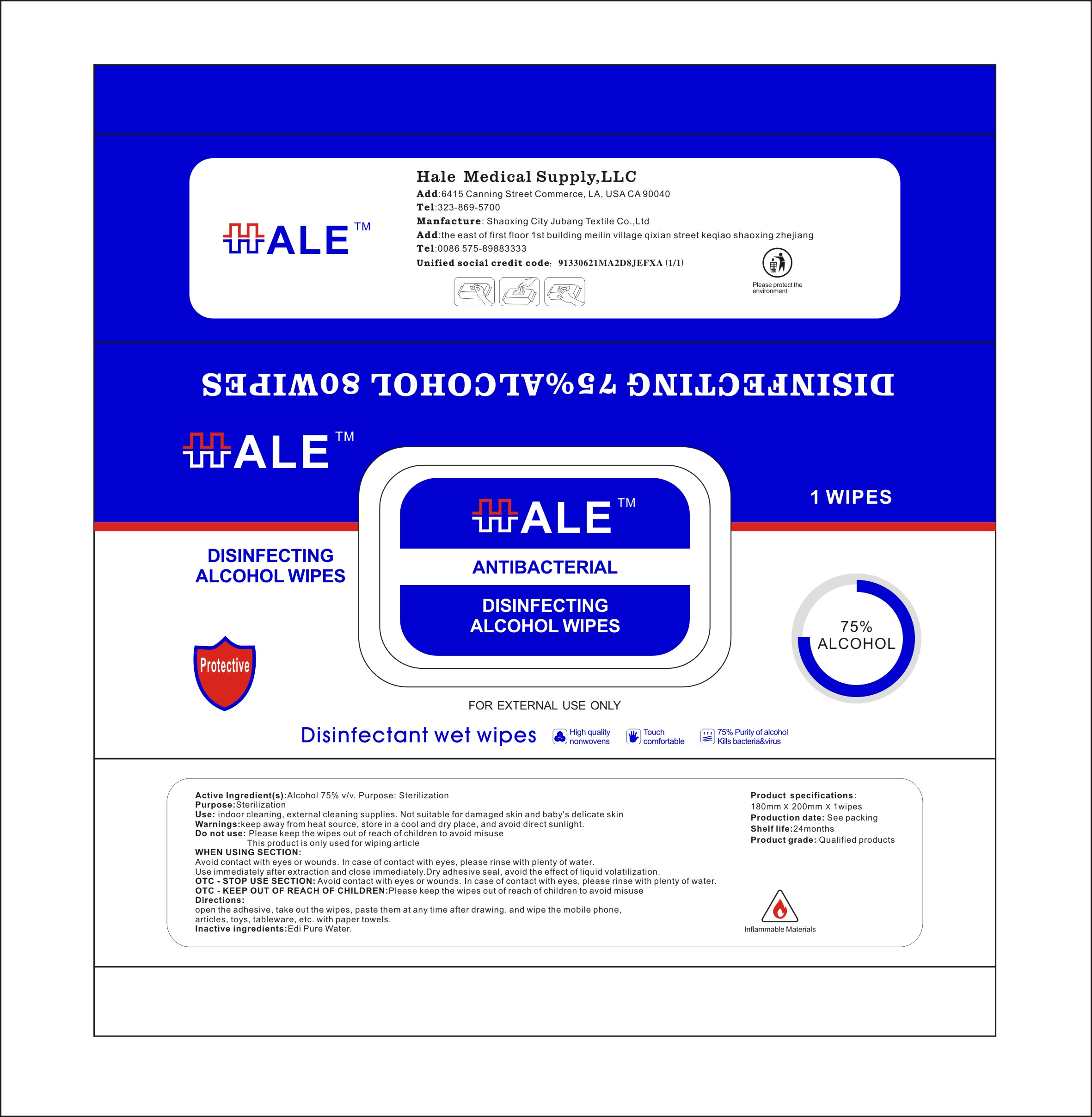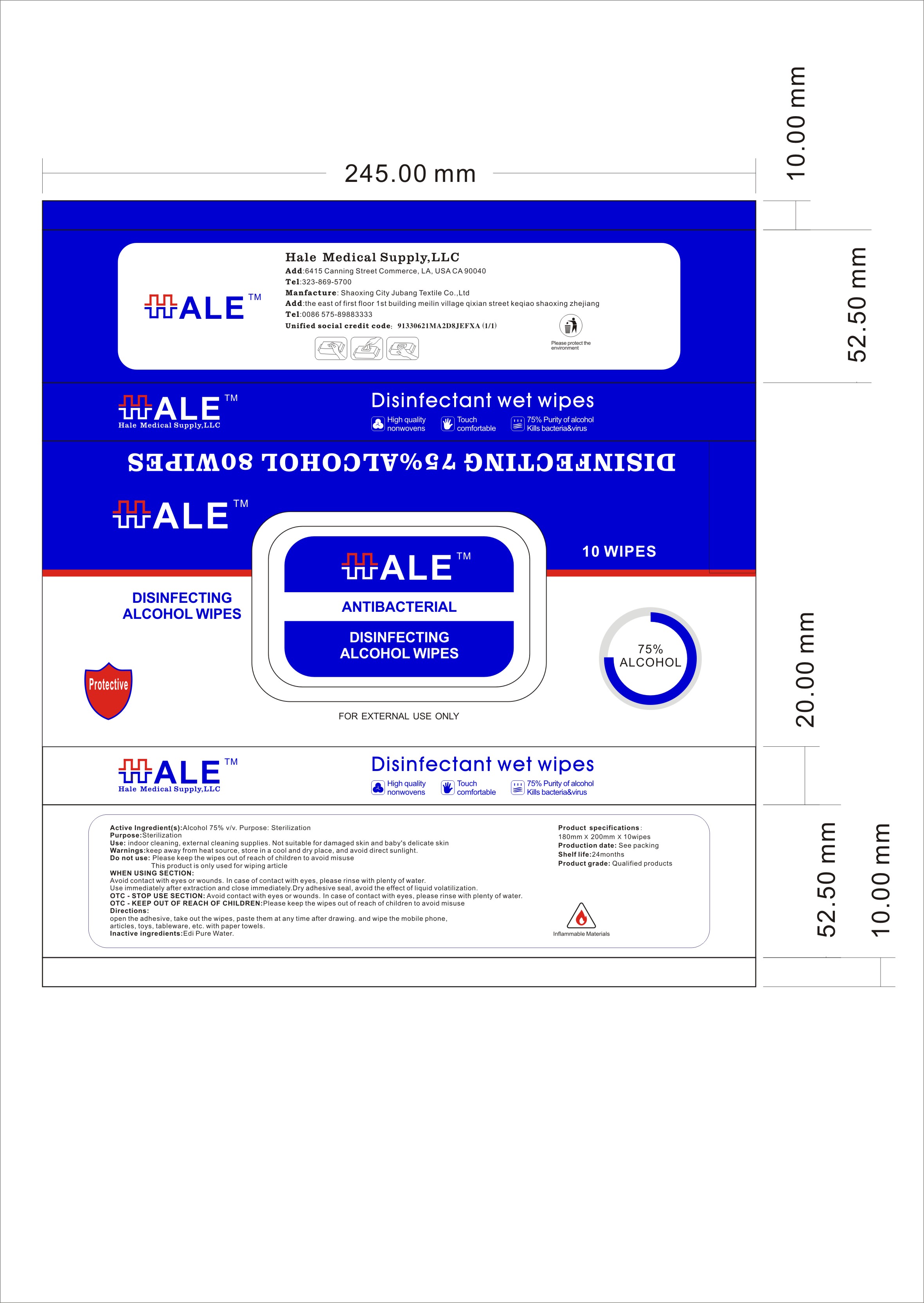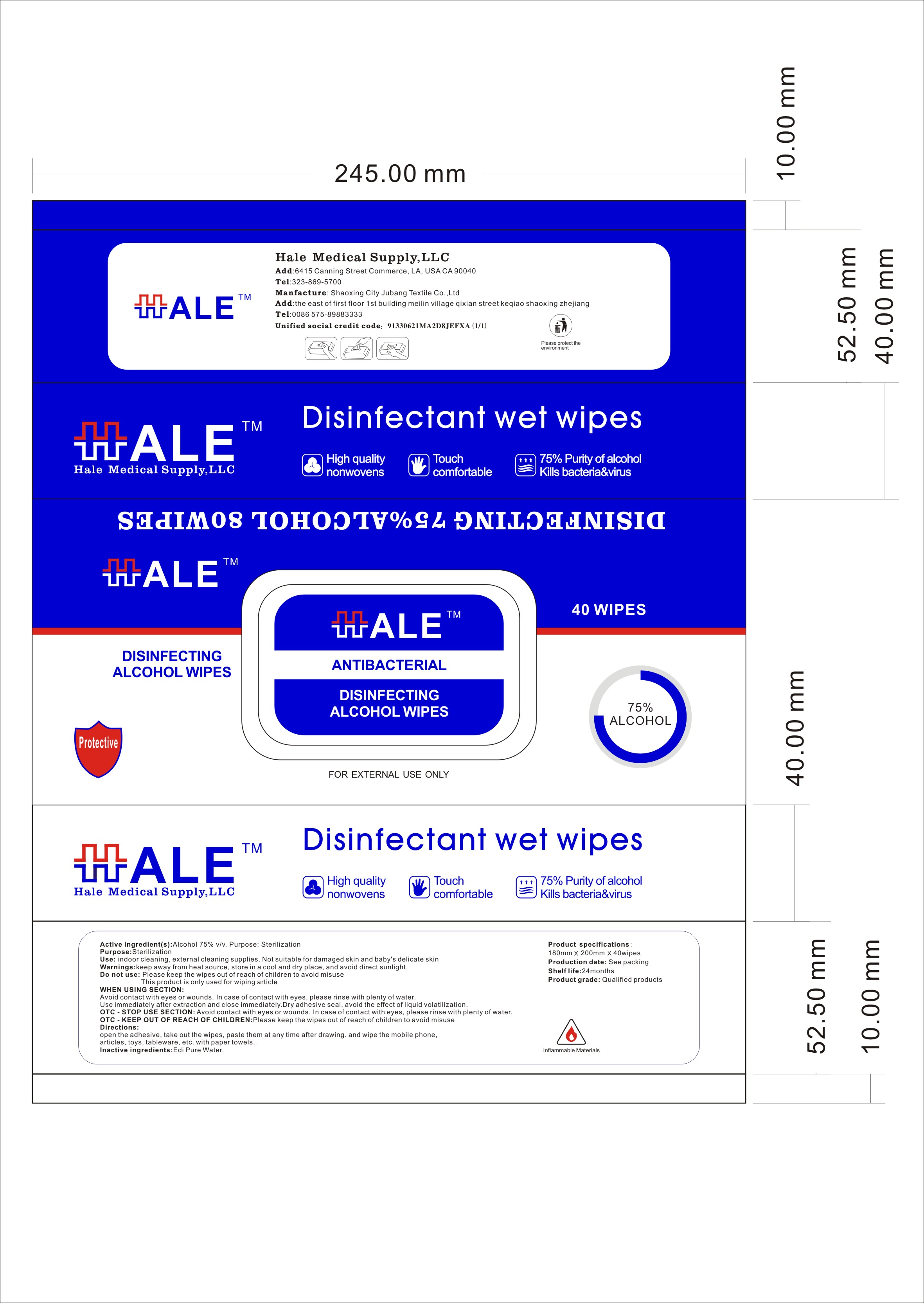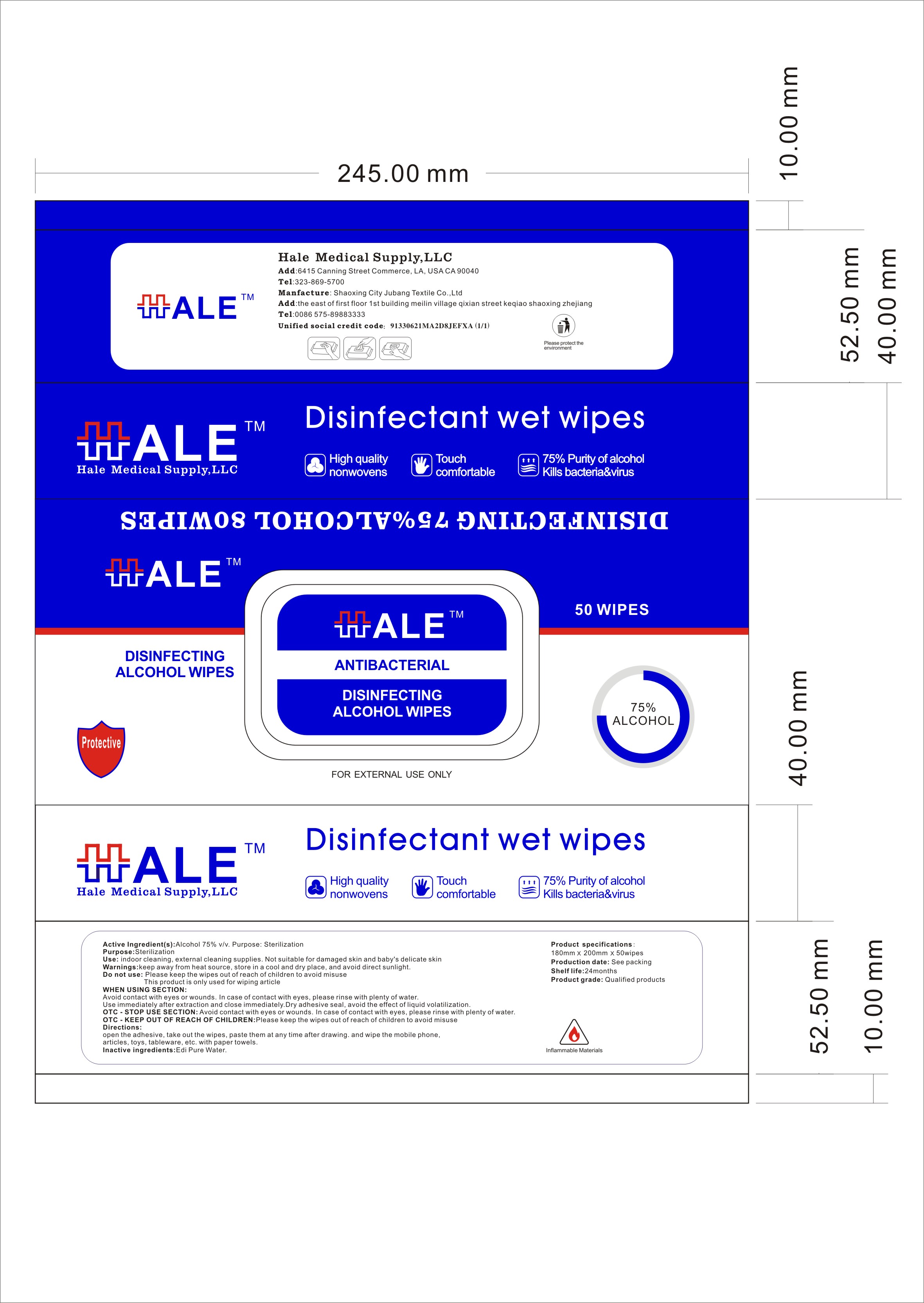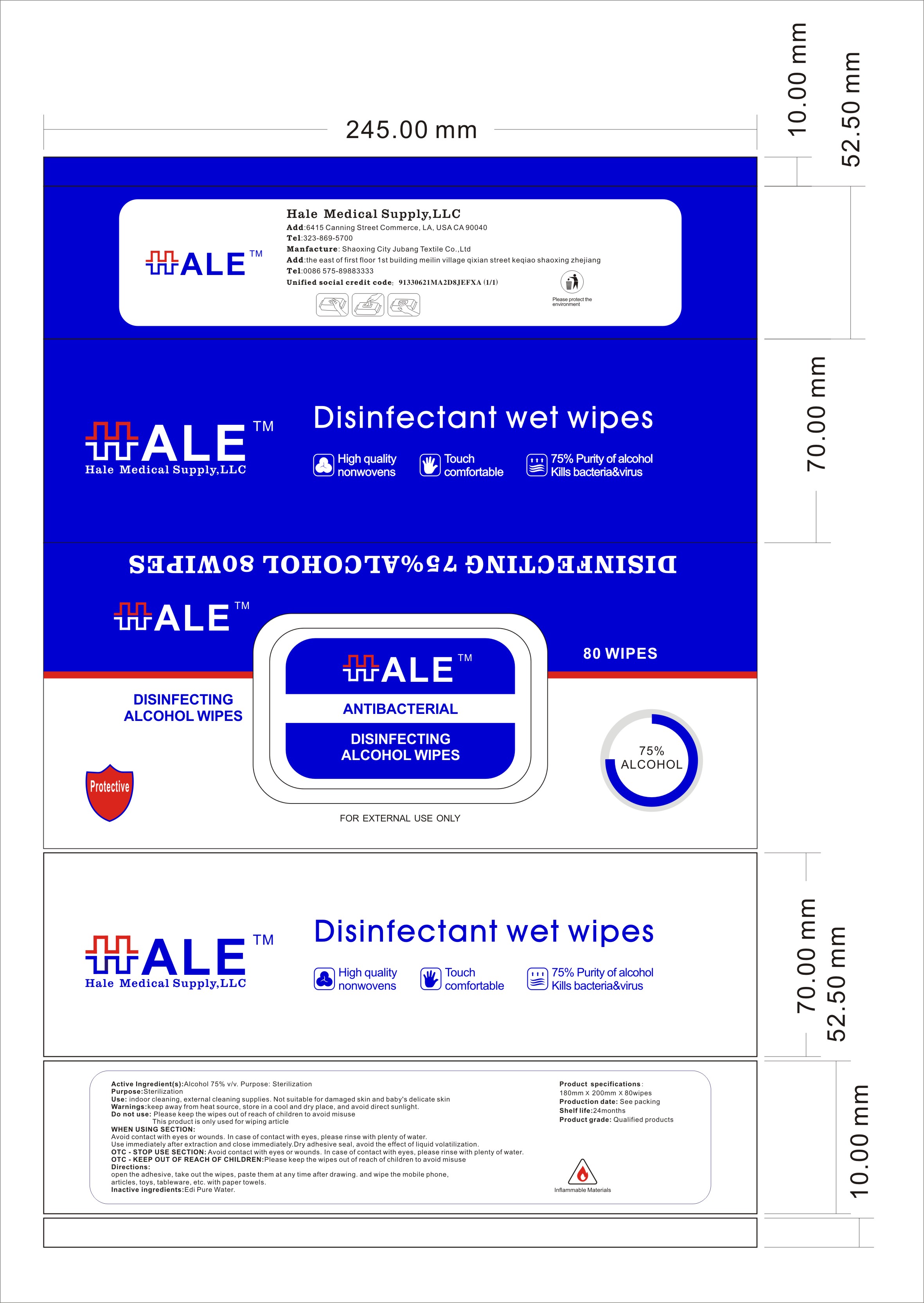 DRUG LABEL: DISINFECTING ALCOHOL WIPES
NDC: 79909-001 | Form: CLOTH
Manufacturer: SHAOXING CITY JUBANG TEXTILE CO.,LTD
Category: otc | Type: HUMAN OTC DRUG LABEL
Date: 20200730

ACTIVE INGREDIENTS: ALCOHOL 75 mL/100 1
INACTIVE INGREDIENTS: WATER

DISINFECTING ALCOHOL WIPES

Active Ingredient(s)

Alcohol 75%V/v

Purpose

Sterilization

Use

indoor cleaning, external cleaning supplies. Not suitable for damaged skin and baby's delicate skin

Warnings

keep away from heat source, store in a cool and dry place, and avoid direct sunlight

Do not use

Please keep the wipes out of reach of children to avoid misuse
This product is only used for wiping article

WHEN USING

Avoid contact with eyes or wounds. In case of contact with eyes, please rinse with plenty of water
Use immediately after extraction and close immediately. Dry adhesive seal, avoid the effect of liquid volatilization

STOP USE

Avoid contact with eyes or wounds. In case of contact with eyes, please rinse with plenty of water.

KEEP OUT OF REACH OF CHILDREN

Please keep the wipes out of reach of children to avoid misuse

Directions

open the adhesive, take out the wipes, paste them at any time after drawing and wipe the mobile phone,articles, toys, tableware, etc with paper towels

Other information

/

Inactive ingredients

Edi Pure Water